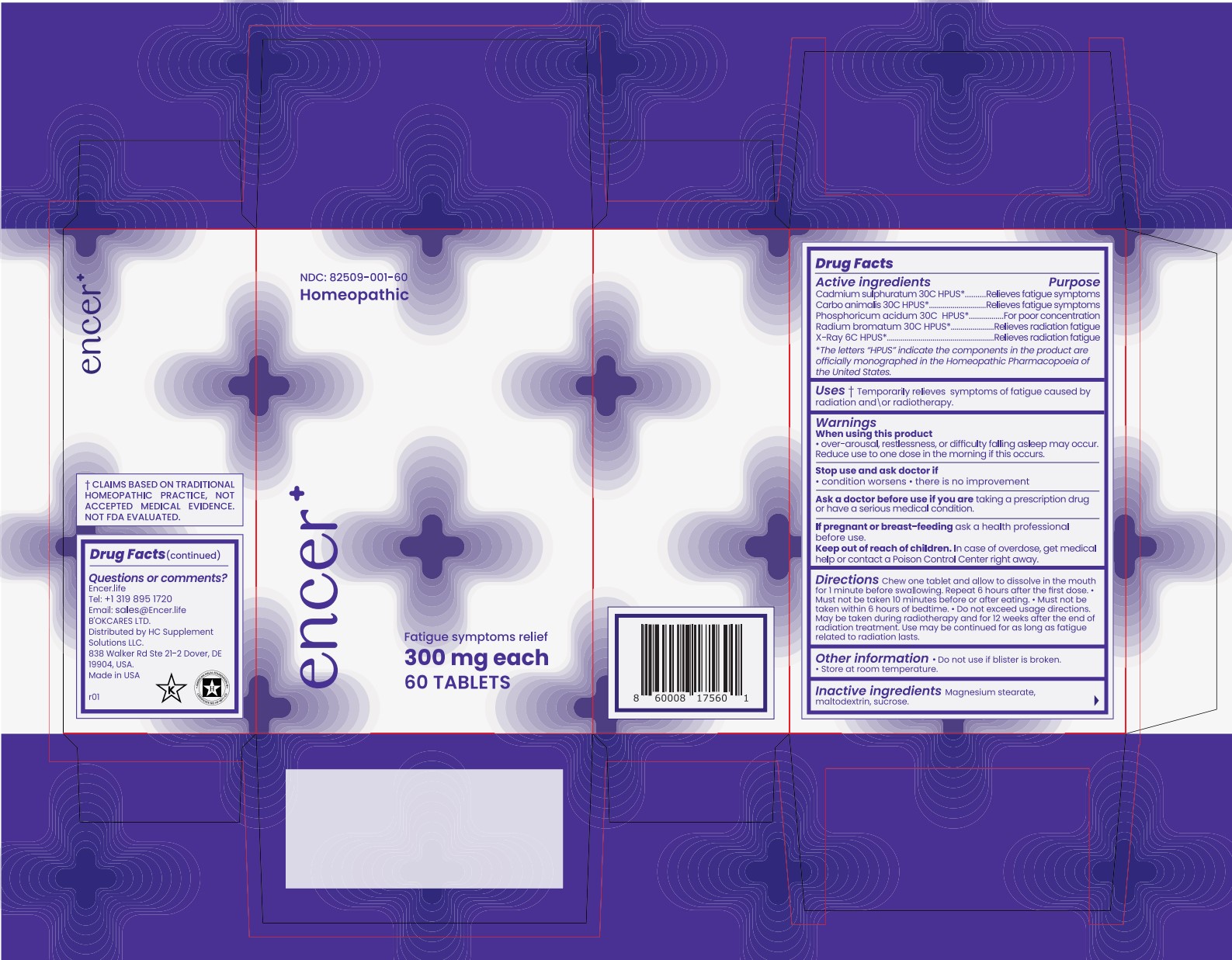 DRUG LABEL: encer
NDC: 82509-001 | Form: TABLET, ORALLY DISINTEGRATING
Manufacturer: B'OKCARES LTD
Category: homeopathic | Type: HUMAN OTC DRUG LABEL
Date: 20251229

ACTIVE INGREDIENTS: CADMIUM SULFIDE 30 [hp_C]/1 1; CARBO ANIMALIS 30 [hp_C]/1 1; PHOSPHORIC ACID 30 [hp_C]/1 1; RADIUM BROMIDE 30 [hp_C]/1 1; ALCOHOL, X-RAY EXPOSED (1000 RAD) 6 [hp_C]/1 1
INACTIVE INGREDIENTS: MAGNESIUM STEARATE; MALTODEXTRIN; SUCROSE

encer

Active Ingredients

Cadmium sulphuratum 30C HPUS*

Carbo animalis 30C HPUS*

Phosphoricum acidum 30C HPUS*

Radium bromatum 30C HPUS*

X-Ray 6C HPUS*

* The letters "HPUS" indicate the components in the product are officially monographed in the Homeopathic Pharmacopoeia of the Unites States.

Purpose

Cadmium sulphuratum 30C HPUS* .... Relieves fatigue symptoms

Carbo animalis 30C HPUS* .... Relieves fatigue symptoms

Phosphoricum acidum 30C HPUS* .... For poor concentration

Radium bromatum 30C HPUS* .... Relieves radiation fatigue

X-Ray 6C HPUS* .... Relieves radiation fatigue

* The letters "HPUS" indicate the components in the product are officially monographed in the Homeopathic Pharmacopoeia of the Unites States.

Uses

Temporarily relieves symptoms of fatigue caused by radiation and\ or radiotherapy.

Warnings

When using this product

- over-arousal, restlessness, or difficulty falling asleep may occur. Reduce use to one dose in the morning if this occurs.

Stop use and ask doctor if

- condition worsens
- there is no improvement

Ask a doctor before use if you are taking a prescription drug or have a serious medical condition.

PREGNANCY OR BREAST FEEDING

If pregnant or breast-feeding ask a health professional before use.

Keep out of reach of children. In case of overdose, get medical help or contact a Poison Control Center right away.

Directions

Chew one tablet and allow to dissolve in the mouth for 1 minute before swallowing. Repeat 6 hours after the first dose.

- Must not be taken 10 minutes before or after eating. • Must not be taken within 6 hours of bedtime. • Do not exceed usage directions. May be taken during radiotherapy and for 12 weeks after the end of radiation treatment. Use may be continued for as long as fatigue related to radiation lasts.

Other information

• Do not use if blister is broken. • Store at room temperature.

Inactive ingredients

Magnesium stearate, maltodextrin, sucrose.

Questions or Comments?

Encer.life

Tel: +1 319 895 1720

Email: sales@Encer.life

B'OKCARES LTD.

Distributed by HC Supplement Solutions LLC

838 Walker Rd Ste 21-2 Dover, DE

19904, USA.

Made in USA

PACKAGE LABEL

NDC: 82509-001-60

Homeopathic

Fatigue symptoms relief

300 mg each

60 TABLETS

PURPOSE

Temporarily relieves symptoms of fatigue cause by radiation and\ or radiotherapy.